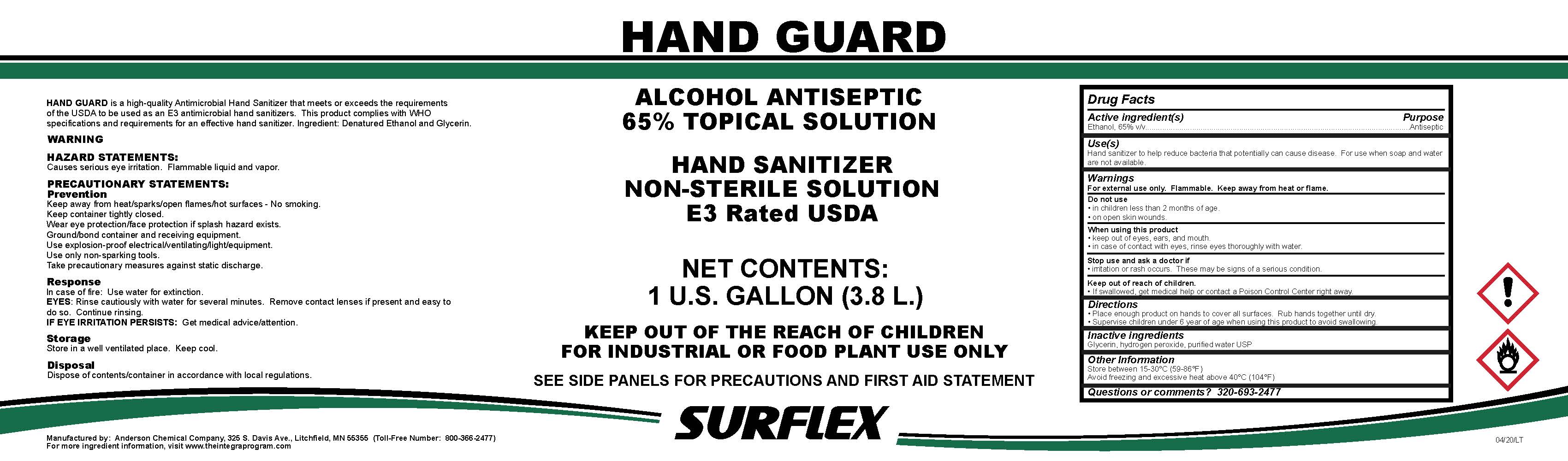 DRUG LABEL: Hand Guard
NDC: 63131-9049 | Form: LIQUID
Manufacturer: Anderson Chemical Company
Category: otc | Type: HUMAN OTC DRUG LABEL
Date: 20200609

ACTIVE INGREDIENTS: ALCOHOL 70 mL/100 mL
INACTIVE INGREDIENTS: GLYCERIN; HYDROGEN PEROXIDE; WATER

Active ingredient

Ethanol, 65% v/v

Purpose

Antiseptic

Use(s)

Hand sanitizer to help reduce bacterial that potentially can cause disease. For use when soap and water are not available.

Warnings

For external use only. Flammable. Keep away from heat or flame.

Do not use

- in children less than 2 months of age.
- on open skin wounds.

When using this product

- keep out of eyes, ears, and mouth
- in case of contact with eyes, rinse eyes thoroughly with water.

Stop use and ask a doctor if

- irritation or rash occurs. These may be signs of a serious condition.

Keep out of reach of children.

- if swallowed, get medical help or contact a Poison Control Center right away.

Directions

- Place enough product on hands to cover all surfaces. Rub hands together until dry.
- Supervise children under 6 years of age when using this product to avoid swallowing.

Inactive ingredients

Glycerin, hydrogen peroxide, purified water USP

Other information

Store between 15-30°C (59-86°F)

Avoid freezing and excessive heat above 40°C (104°F)

Questions or comments?

320-693-2477

Principal Display Panel

3785 ml NDC: 63131-9049